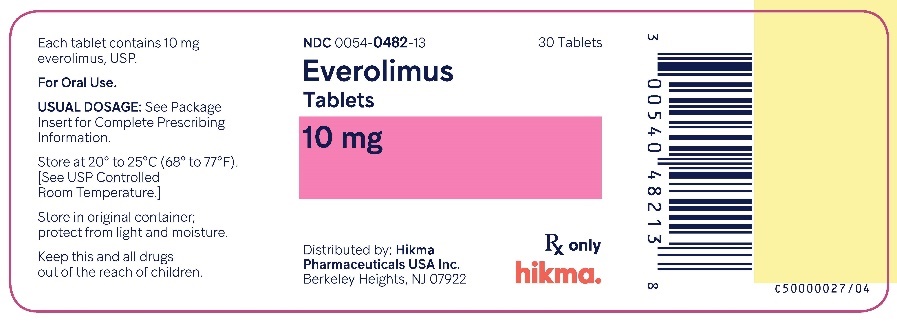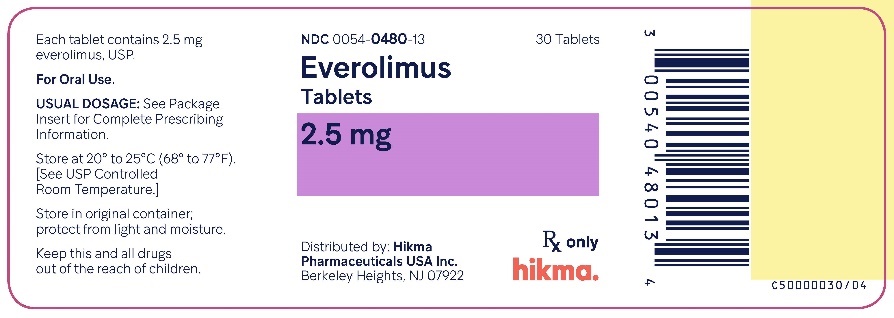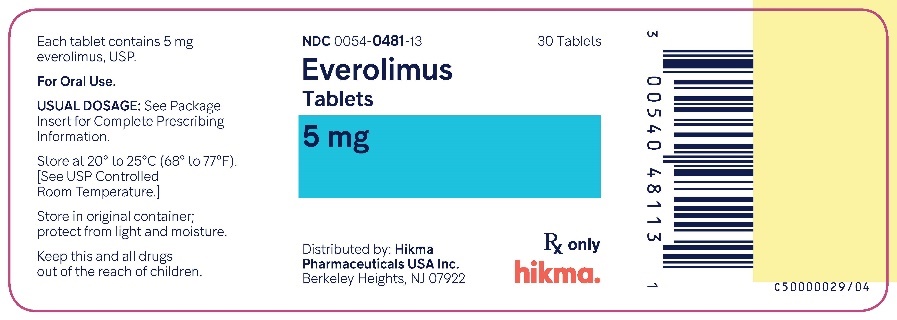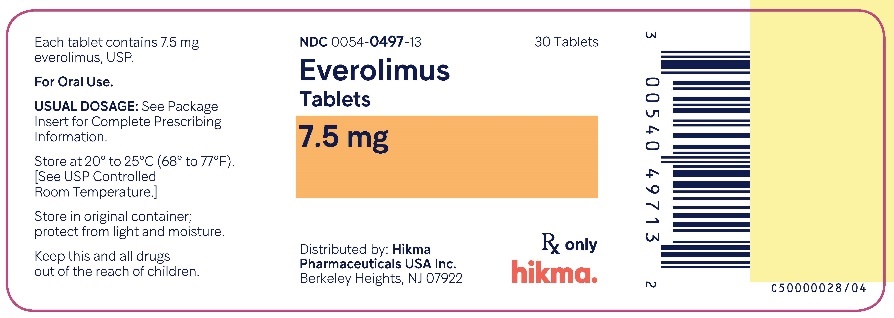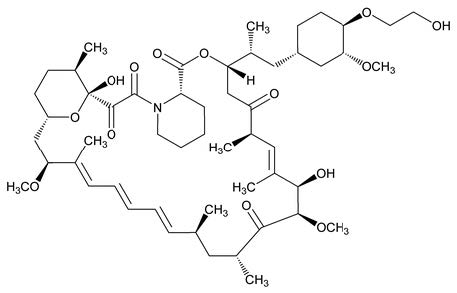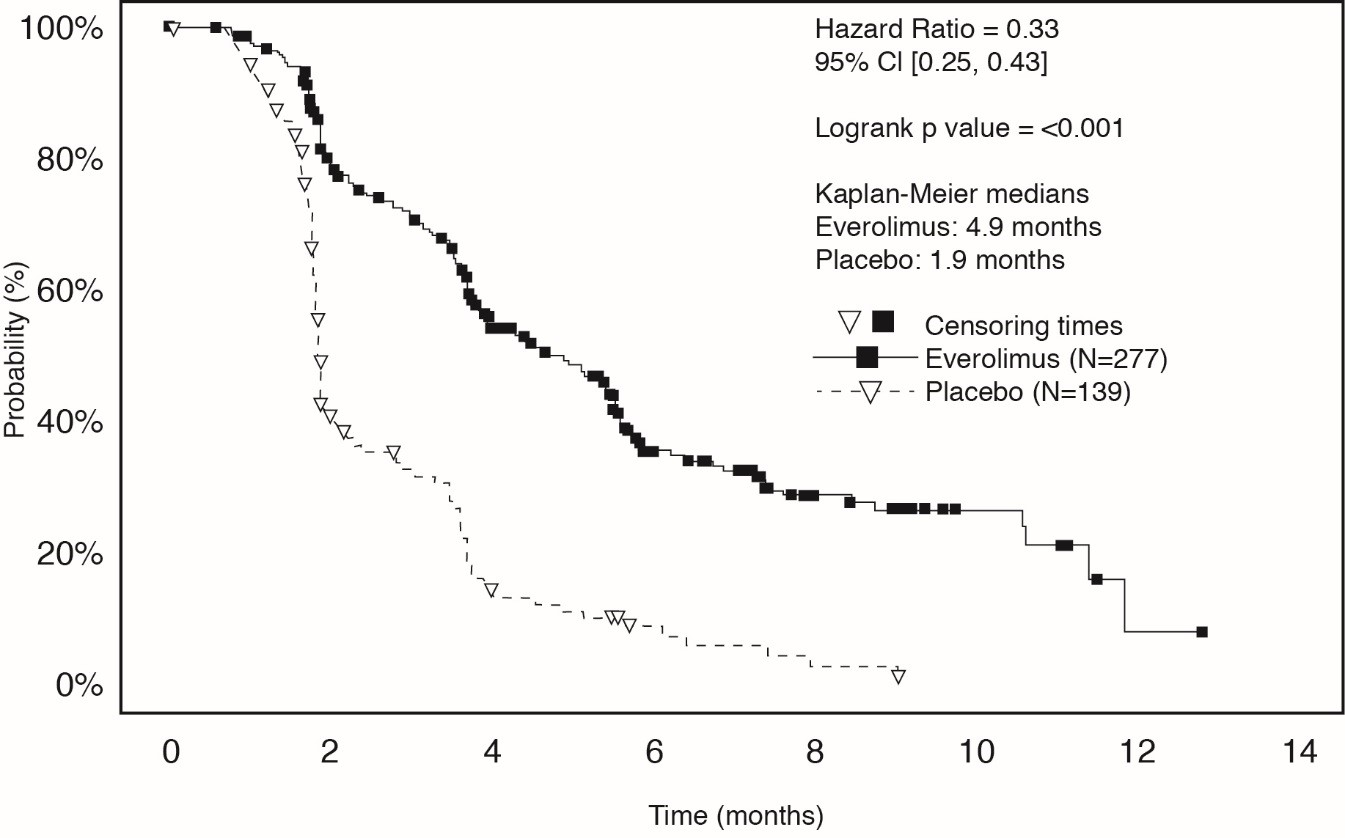 DRUG LABEL: Everolimus
NDC: 0054-0480 | Form: TABLET
Manufacturer: Hikma Pharmaceuticals USA Inc.
Category: prescription | Type: HUMAN PRESCRIPTION DRUG LABEL
Date: 20240423

ACTIVE INGREDIENTS: EVEROLIMUS 2.5 mg/1 1
INACTIVE INGREDIENTS: BUTYLATED HYDROXYTOLUENE; CROSPOVIDONE (120 .MU.M); HYPROMELLOSE 2910 (5 MPA.S); ANHYDROUS LACTOSE; MAGNESIUM STEARATE

HIGHLIGHTS OF PRESCRIBING INFORMATION

These highlights do not include all the information needed to use EVEROLIMUS TABLETS safely and effectively. See full prescribing information for EVEROLIMUS TABLETS.
EVEROLIMUS tablets, for oral use
Initial U.S. Approval: 2009

1 INDICATIONS AND USAGE

Everolimus is a kinase inhibitor indicated for the treatment of:

- Adults with advanced renal cell carcinoma (RCC) after failure of treatment with sunitinib or sorafenib. (1.3)
- Adults with renal angiomyolipoma and tuberous sclerosis complex (TSC), not requiring immediate surgery. (1.4)

2 DOSAGE AND ADMINISTRATION

Modify the dose for patients with hepatic impairment or for patients taking drugs that inhibit or induce P-glycoprotein (P-gp) and CYP3A4. (2.1)

RCC:

- 10 mg orally once daily (2.4)

TSC-Associated Renal Angiomyolipoma:

- 10 mg orally once daily. (2.5)

3 DOSAGE FORMS AND STRENGTHS

Everolimus Tablets: 2.5 mg, 5 mg, 7.5 mg, and 10 mg tablets. (3)

4 CONTRAINDICATIONS

Clinically significant hypersensitivity to everolimus or to other rapamycin derivatives. (4)

5 WARNINGS AND PRECAUTIONS

- Non-infectious Pneumonitis: Monitor for clinical symptoms or radiological changes. Withhold or permanently discontinue based on severity. (2.9, 5.1)
- Infections: Monitor for signs and symptoms of infection. Withhold or permanently discontinue based on severity. (2.9, 5.2)
- Severe Hypersensitivity Reactions: Permanently discontinue for clinically significant hypersensitivity. (5.3)
- Angioedema: Patients taking concomitant angiotensin-converting-enzyme (ACE) inhibitors may be at increased risk for angioedema. Permanently discontinue for angioedema. (5.4, 7.2)
- Stomatitis: Initiate dexamethasone alcohol-free mouthwash when starting treatment. (5.5, 6.1)
- Renal Failure: Monitor renal function prior to treatment and periodically thereafter. (5.6)
- Risk of Impaired Wound Healing: Withhold for at least 1 week prior to elective surgery. Do not administer for at least 2 weeks following major surgery and until adequate wound healing. The safety of resumption of treatment after resolution of wound healing complications has not been established. (5.7)
- Metabolic Disorders: Monitor serum glucose and lipids prior to treatment and periodically thereafter. Withhold or permanently discontinue based on severity. (2.9, 5.9)
- Myelosuppression: Monitor hematologic parameters prior to treatment and periodically thereafter. Withhold or permanently discontinue based on severity. (2.9, 5.10)
- Risk of Infection or Reduced Immune Response with Vaccination: Avoid live vaccines and close contact with those who have received live vaccines. Complete recommended childhood vaccinations prior to starting treatment. (5.11)
- Radiation Sensitization and Radiation Recall: Severe radiation reactions may occur. (5.12, 6.2)
- Embryo-Fetal Toxicity: Can cause fetal harm. Advise patients of reproductive potential of the potential risk to a fetus and to use effective contraception. (5.13, 8.1, 8.3)

6 ADVERSE REACTIONS

- RCC: Most common adverse reactions (incidence ≥30%) include stomatitis, infections, rash, fatigue, diarrhea, edema, abdominal pain, nausea, fever, asthenia, cough, headache and decreased appetite. (6.1)
- TSC-Associated Renal Angiomyolipoma: Most common adverse reaction (incidence ≥ 30%) is stomatitis. (6.1)

To report SUSPECTED ADVERSE REACTIONS, contact Hikma Pharmaceuticals USA Inc. at 1-800-962-8364 or FDA at 1-800-FDA-1088 or www.fda.gov/medwatch.

7 DRUG INTERACTIONS

- P-gp and strong CYP3A4 Inhibitors: Avoid concomitant use. (2.11, 7.1)
- P-gp and moderate CYP3A4 Inhibitors: Reduce the dose as recommended. (2.11, 7.1)
- P-gp and strong CYP3A4 Inducers: Increase the dose as recommended. (2.12, 7.1)

8 USE IN SPECIFIC POPULATIONS

- For RCC or TSC-associated renal angiomyolipoma patients with hepatic impairment, reduce the dose. (2.10, 8.6)

FULL PRESCRIBING INFORMATION

1 INDICATIONS AND USAGE

1.3 Renal Cell Carcinoma (RCC)

Everolimus is indicated for the treatment of adult patients with advanced RCC after failure of treatment with sunitinib or sorafenib.

1.4 Tuberous Sclerosis Complex (TSC)-Associated Renal Angiomyolipoma

Everolimus is indicated for the treatment of adult patients with renal angiomyolipoma and TSC, not requiring immediate surgery.

2 DOSAGE AND ADMINISTRATION

Everolimus is available in tablets for oral administration

2.1 Important Dosage Information

- Modify the dosage for patients with hepatic impairment or for patients taking drugs that inhibit or induce P-glycoprotein (P-gp) and CYP3A4 [see Dosage and Administration (2.11, 2.12)].

2.4 Recommended Dosage for Renal Cell Carcinoma (RCC)

The recommended dosage of Everolimus is 10 mg orally once daily until disease progression or unacceptable toxicity.

2.5 Recommended Dosage for Tuberous Sclerosis Complex (TSC)-Associated Renal Angiomyolipoma

The recommended dosage of Everolimus is 10 mg orally once daily until disease progression or unacceptable toxicity.

2.9 Dosage Modifications for Adverse Reactions

Table 2 summarizes recommendations for dosage modifications of Everolimus for the management of adverse reactions.

Table 2: Recommended Dosage Modifications for Everolimus for Adverse Reactions

Adverse Reaction | Severity | Dosage Modification
Non-infectious pneumonitis [see Warnings and Precautions (5.1)] | Grade 2 | Withhold until improvement to Grade 0 or 1. Resume at 50% of previous dose; change to every other day dosing if the reduced dose is lower than the lowest available strength. Permanently discontinue if toxicity does not resolve or improve to Grade 1 within 4 weeks.
 | Grade 3 | Withhold until improvement to Grade 0 or 1. Resume at 50% of previous dose; change to every other day dosing if the reduced dose is lower than the lowest available strength. If toxicity recurs at Grade 3, permanently discontinue.
 | Grade 4 | Permanently discontinue.
Stomatitis [see Warnings and Precautions (5.5)] | Grade 2 | Withhold until improvement to Grade 0 or 1. Resume at same dose. If recurs at Grade 2, withhold until improvement to Grade 0 or 1. Resume at 50% of previous dose; change to every other day dosing if the reduced dose is lower than the lowest available strength.
 | Grade 3 | Withhold until improvement to Grade 0 or 1. Resume at 50% of previous dose; change to every other day dosing if the reduced dose is lower than the lowest available strength.
 | Grade 4 | Permanently discontinue.
Metabolic events (e.g., hyperglycemia, dyslipidemia) [see Warnings and Precautions (5.9)] | Grade 3 | Withhold until improvement to Grade 0, 1, or 2. Resume at 50% of previous dose; change to every other day dosing if the reduced dose is lower than the lowest available strength.
 | Grade 4 | Permanently discontinue.
Other non-hematologic toxicities | Grade 2 | If toxicity becomes intolerable, withhold until improvement to Grade 0 or 1. Resume at same dose. If toxicity recurs at Grade 2, withhold until improvement to Grade 0 or 1. Resume at 50% of previous dose; change to every other day dosing if the reduced dose is lower than the lowest available strength.
 | Grade 3 | Withhold until improvement to Grade 0 or 1. Consider resuming at 50% of previous dose; change to every other day dosing if the reduced dose is lower than the lowest available strength. If recurs at Grade 3, permanently discontinue.
 | Grade 4 | Permanently discontinue.
Thrombocytopenia [see Warnings and Precautions (5.10)] | Grade 2 | Withhold until improvement to Grade 0 or 1. Resume at same dose.
 | Grade 3 OR Grade 4 | Withhold until improvement to Grade 0 or 1. Resume at 50% of previous dose; change to every other day dosing if the reduced dose is lower than the lowest available strength.
Neutropenia [see Warnings and Precautions (5.10)] | Grade 3 | Withhold until improvement to Grade 0, 1, or 2. Resume at same dose.
 | Grade 4 | Withhold until improvement to Grade 0, 1, or 2. Resume at 50% of previous dose; change to every other day dosing if the reduced dose is lower than the lowest available strength.
Febrile neutropenia [see Warnings and Precautions (5.10)] | Grade 3 | Withhold until improvement to Grade 0, 1, or 2, and no fever. Resume at 50% of previous dose; change to every other day dosing if the reduced dose is lower than the lowest available strength.
 | Grade 4 | Permanently discontinue.

2.10 Dosage Modifications for Hepatic Impairment

The recommended dosages of Everolimus for patients with hepatic impairment are described in Table 3 [see Use in Specific Populations (8.6)]:

Table 3: Recommended Dosage Modifications for Patients with Hepatic Impairment

Indication | Dose Modification for Everolimus
RCC and TSC-Associated Renal Angiomyolipoma | - Mild hepatic impairment (Child-Pugh class A) – 7.5 mg orally once daily; decrease the dose to 5 mg orally once daily if a dose of 7.5 mg once daily is not tolerated. - Moderate hepatic impairment (Child-Pugh class B) – 5 mg orally once daily; decrease the dose to 2.5 mg orally once daily if a dose of 5 mg once daily is not tolerated. - Severe hepatic impairment (Child-Pugh class C) – 2.5 mg orally once daily if the desired benefit outweighs the risk; do not exceed a dose of 2.5 mg once daily.

Abbreviations: RCC, Renal Cell Carcinoma; TSC, Tuberous Sclerosis Complex.

2.11 Dosage Modifications for P-gp and CYP3A4 Inhibitors

- Avoid the concomitant use of P-gp and strong CYP3A4 inhibitors [see Drug Interactions (7.1)].
- Avoid ingesting grapefruit and grapefruit juice.
- Reduce the dose for patients taking Everolimus with a P-gp and moderate CYP3A4 inhibitor as recommended in Table 4 [see Drug Interactions (7.1), Clinical Pharmacology (12.3)].

Table 4: Recommended Dosage Modifications for Concurrent Use of Everolimus with a P-gp and Moderate CYP3A4 Inhibitor

Indication | Dose Modification for Everolimus
RCC and TSC-Associated Renal Angiomyolipoma | - Reduce dose to 2.5 mg once daily. - May increase dose to 5 mg once daily if tolerated. - Resume dose administered prior to inhibitor initiation, once the inhibitor is discontinued for 3 days.

2.12 Dosage Modifications for P-gp and CYP3A4 Inducers

- Avoid concomitant use of St. John’s Wort (Hypericum perforatum).
- Increase the dose for patients taking Everolimus with a P-gp and strong CYP3A4 inducer as recommended in Table 5 [see Drug Interactions (7.1), Clinical Pharmacology (12.3)].

Table 5: Recommended Dosage Modifications for Concurrent Use of Everolimus with P-gp and Strong CYP3A4 Inducers

Indication | Dose Modification for Everolimus
RCC and TSC-Associated Renal Angiomyolipoma | - Avoid coadministration where alternatives exist. - If coadministration cannot be avoided, double the daily dose using increments of 5 mg or less. Multiple increments may be required. - Resume the dose administered prior to inducer initiation, once an inducer is discontinued for 5 days.

2.13 Administration and Preparation

- Administer Everolimus at the same time each day.
- Administer Everolimus consistently either with or without food [see Clinical Pharmacology (12.3)].
- If a dose of Everolimus is missed, it can be administered up to 6 hours after the time it is normally administered. After more than 6 hours, the dose should be skipped for that day. The next day, Everolimus should be administered at its usual time. Double doses should not be administered to make up for the dose that was missed.
- Everolimus should be swallowed whole with a glass of water. Do not break or crush tablets.

3 DOSAGE FORMS AND STRENGTHS

Everolimus tablets are available as 2.5 mg, 5 mg, 7.5 mg, and 10 mg tablets for oral administration.

4 CONTRAINDICATIONS

Everolimus is contraindicated in patients with clinically significant hypersensitivity to everolimus or to other rapamycin derivatives [see Warnings and Precautions (5.3)].

5 WARNINGS AND PRECAUTIONS

5.1 Non-infectious Pneumonitis

Non-infectious pneumonitis is a class effect of rapamycin derivatives. Non-infectious pneumonitis was reported in up to 19% of patients treated with Everolimus in clinical trials, some cases were reported with pulmonary hypertension (including pulmonary arterial hypertension) as a secondary event. The incidence of Grade 3 and 4 non-infectious pneumonitis was up to 4% and up to 0.2%, respectively [see Adverse Reactions (6.1)]. Fatal outcomes have been observed.

Consider a diagnosis of non-infectious pneumonitis in patients presenting with non-specific respiratory signs and symptoms. Consider opportunistic infections such as pneumocystis jiroveci pneumonia (PJP) in the differential diagnosis. Advise patients to report promptly any new or worsening respiratory symptoms.

Continue Everolimus without dose alteration in patients who develop radiological changes suggestive of non-infectious pneumonitis and have few or no symptoms. Imaging appears to overestimate the incidence of clinical pneumonitis.

For Grade 2 to 4 non-infectious pneumonitis, withhold or permanently discontinue Everolimus based on severity [see Dosage and Administration (2.9)]. Corticosteroids may be indicated until clinical symptoms resolve. Administer prophylaxis for PJP when concomitant use of corticosteroids or other immunosuppressive agents are required. The development of pneumonitis has been reported even at a reduced dose.

5.2 Infections

Everolimus has immunosuppressive properties and may predispose patients to bacterial, fungal, viral, or protozoal infections, including infections with opportunistic pathogens [see Adverse Reactions (6.1)]. Localized and systemic infections, including pneumonia, mycobacterial infections, other bacterial infections, invasive fungal infections (e.g., aspergillosis, candidiasis, or PJP), and viral infections (e.g., reactivation of hepatitis B virus) have occurred. Some of these infections have been severe (e.g., sepsis, septic shock, or resulting in multisystem organ failure) or fatal. The incidence of Grade 3 and 4 infections was up to 10% and up to 3%, respectively.

Complete treatment of preexisting invasive fungal infections prior to starting treatment. Monitor for signs and symptoms of infection. Withhold or permanently discontinue Everolimus based on severity of infection [see Dosage and Administration (2.9)].

Administer prophylaxis for PJP when concomitant use of corticosteroids or other immunosuppressive agents are required.

5.3 Severe Hypersensitivity Reactions

Hypersensitivity reactions to Everolimus have been observed and include anaphylaxis, dyspnea, flushing, chest pain, and angioedema (e.g., swelling of the airways or tongue, with or without respiratory impairment) [see Contraindications (4)]. The incidence of Grade 3 hypersensitivity reactions was up to 1%. Permanently discontinue Everolimus for the development of clinically significant hypersensitivity.

5.4 Angioedema with Concomitant Use of Angiotensin-Converting Enzyme (ACE) Inhibitors

Patients taking concomitant ACE inhibitors with Everolimus may be at increased risk for angioedema (e.g., swelling of the airways or tongue, with or without respiratory impairment). In a pooled analysis of randomized double-blind oncology clinical trials, the incidence of angioedema in patients taking Everolimus with an ACE inhibitor was 6.8% compared to 1.3% in the control arm with an ACE inhibitor. Permanently discontinue Everolimus for angioedema.

5.5 Stomatitis

Stomatitis, including mouth ulcers and oral mucositis, has occurred in patients treated with Everolimus at an incidence ranging from 44% to 78% across clinical trials. Grades 3-4 stomatitis was reported in 4% to 9% of patients [see Adverse Reactions (6.1)]. Stomatitis most often occurs within the first 8 weeks of treatment. When starting Everolimus, initiating dexamethasone alcohol-free oral solution as a swish and spit mouthwash reduces the incidence and severity of stomatitis [see Adverse Reactions (6.1)]. If stomatitis does occur, mouthwashes and/or other topical treatments are recommended. Avoid alcohol-, hydrogen peroxide-, iodine-, or thyme- containing products, as they may exacerbate the condition. Do not administer antifungal agents, unless fungal infection has been diagnosed.

5.6 Renal Failure

Cases of renal failure (including acute renal failure), some with a fatal outcome, have occurred in patients taking Everolimus. Elevations of serum creatinine and proteinuria have been reported in patients taking Everolimus [see Adverse Reactions (6.1)]. The incidence of Grade 3 and 4 elevations of serum creatinine was up to 2% and up to 1%, respectively. The incidence of Grade 3 and 4 proteinuria was up to 1% and up to 0.5%, respectively. Monitor renal function prior to starting Everolimus and annually thereafter. Monitor renal function at least every 6 months in patients who have additional risk factors for renal failure.

5.7 Risk of Impaired Wound Healing

Impaired wound healing can occur in patients who receive drugs that inhibit the VEGF signaling pathway. Therefore, Everolimus has the potential to adversely affect wound healing.

Withhold Everolimus for at least 1 week prior to elective surgery. Do not administer for at least 2 weeks following major surgery and until adequate wound healing. The safety of resumption of treatment upon resolution of wound healing complications has not been established.

5.9 Metabolic Disorders

Hyperglycemia, hypercholesterolemia, and hypertriglyceridemia have been reported in patients taking Everolimus at an incidence up to 75%, 86%, and 73%, respectively. The incidence of these Grade 3 and 4 laboratory abnormalities was up to 15% and up to 0.4%, respectively [see Adverse Reactions (6.1)]. In non-diabetic patients, monitor fasting serum glucose prior to starting Everolimus and annually thereafter. In diabetic patients, monitor fasting serum glucose more frequently as clinically indicated. Monitor lipid profile prior to starting Everolimus and annually thereafter. When possible, achieve optimal glucose and lipid control prior to starting Everolimus. For Grade 3 to 4 metabolic events, withhold or permanently discontinue Everolimus based on severity [see Dosage and Administration (2.9)].

5.10 Myelosuppression

Anemia, lymphopenia, neutropenia, and thrombocytopenia have been reported in patients taking Everolimus. The incidence of these Grade 3 and 4 laboratory abnormalities was up to 16% and up to 2%, respectively [see Adverse Reactions (6.1)]. Monitor complete blood count (CBC) prior to starting Everolimus every 6 months for the first year of treatment and annually thereafter. Withhold or permanently discontinue Everolimus based on severity [see Dosage and Administration (2.9)].

5.11 Risk of Infection or Reduced Immune Response with Vaccination

The safety of immunization with live vaccines during Everolimus therapy has not been studied. Due to the potential increased risk of infection, avoid the use of live vaccines and close contact with individuals who have received live vaccines during treatment with Everolimus. Due to the potential increased risk of infection or reduced immune response with vaccination, complete the recommended childhood series of vaccinations according to American Council on Immunization Practices (ACIP) guidelines prior to the start of therapy. An accelerated vaccination schedule may be appropriate.

5.12 Radiation Sensitization and Radiation Recall

Radiation sensitization and recall, in some cases severe, involving cutaneous and visceral organs (including radiation esophagitis and pneumonitis) have been reported in patients treated with radiation prior to, during, or subsequent to everolimus treatment [see Adverse Reactions (6.2)].

Monitor patients closely when everolimus is administered during or sequentially with radiation treatment.

5.13 Embryo-Fetal Toxicity

Based on animal studies and the mechanism of action, Everolimus can cause fetal harm when administered to a pregnant woman. In animal studies, everolimus caused embryo-fetal toxicities in rats when administered during the period of organogenesis at maternal exposures that were lower than human exposures at the clinical dose of 10 mg once daily. Advise pregnant women of the potential risk to a fetus. Advise female patients of reproductive potential to avoid becoming pregnant and to use effective contraception during treatment with Everolimus and for 8 weeks after the last dose. Advise male patients with female partners of reproductive potential to use effective contraception during treatment with Everolimus and for 4 weeks after the last dose [see Use in Specific Populations (8.1, 8.3)].

6 ADVERSE REACTIONS

The following serious adverse reactions are described elsewhere in the labeling:

- Non-infectious Pneumonitis [see Warnings and Precautions (5.1)].
- Infections [see Warnings and Precautions (5.2)].
- Severe Hypersensitivity Reactions [see Warnings and Precautions (5.3)].
- Angioedema with Concomitant Use of ACE Inhibitors [see Warnings and Precautions (5.4)].
- Stomatitis [see Warnings and Precautions (5.5)].
- Renal Failure [see Warnings and Precautions (5.6)].
- Impaired Wound Healing [see Warnings and Precautions (5.7)].
- Metabolic Disorders [see Warnings and Precautions (5.9)].
- Myelosuppression [see Warnings and Precautions (5.10)].
- Radiation Sensitization and Radiation Recall [see Warnings and Precautions (6.2)].

6.1 Clinical Trials Experience

Because clinical trials are conducted under widely varying conditions, the adverse reaction rates observed cannot be directly compared to rates in other trials and may not reflect the rates observed in clinical practice.

The data described below reflect exposure to Everolimus (n=274) and placebo (n=137) in a randomized, controlled trial (RECORD-1) in patients with metastatic RCC who received prior treatment with sunitinib and/or sorafenib. The median age of patients was 61 years (27 to 85 years), 88% were white, and 78% were male. The median duration of blinded study treatment was 141 days (19 to 451 days) for patients receiving Everolimus.

The most common adverse reactions (incidence ≥30%) were stomatitis, infections, asthenia, fatigue, cough, and diarrhea. The most common Grade 3 to 4 adverse reactions (incidence ≥3%) were infections, dyspnea, fatigue, stomatitis, dehydration, pneumonitis, abdominal pain, and asthenia. The most common laboratory abnormalities (incidence ≥50%) were anemia, hypercholesterolemia, hypertriglyceridemia, hyperglycemia, lymphopenia, and increased creatinine. The most common Grade 3 to 4 laboratory abnormalities (incidence ≥3%) were lymphopenia, hyperglycemia, anemia, hypophosphatemia, and hypercholesterolemia.

Deaths due to acute respiratory failure (0.7%), infection (0.7%), and acute renal failure (0.4%) were observed on the Everolimus arm. The rate of adverse reactions resulting in permanent discontinuation was 14% for the Everolimus group. The most common adverse reactions leading to treatment discontinuation were pneumonitis and dyspnea. Infections, stomatitis, and pneumonitis were the most common reasons for treatment delay or dose reduction. The most common medical interventions required during Everolimus treatment were for infections, anemia, and stomatitis.

Adverse reactions reported with an incidence of ≥ 10% for patients receiving Everolimus vs. placebo are presented in Table 12. Laboratory abnormalities are presented in Table 13.

Table 12: Adverse Reactions Reported in ≥ 10% of Patients with RCC and at a Higher Rate in the Everolimus Arm than in the Placebo Arm in RECORD-1

 |  | Everolimus N = 274 |  | Placebo N = 137
 | All Grades |  | Grades 3-4 | All Grades | Grades 3-4
 |  | % | % | % | %
Gastrointestinal
Stomatitis [Stomatitis (including aphthous stomatitis), and mouth and tongue ulceration.] |  | 44 | 4 | 8 | 0
Diarrhea |  | 30 | 2 [No Grade 4 adverse reactions were reported.] | 7 | 0
Nausea |  | 26 | 2 | 19 | 0
Vomiting |  | 20 | 2 | 12 | 0
Infections [Includes all reported infections including, but not limited to, respiratory tract (upper and lower) infections, urinary tract infections, and skin infections.] |  | 37 | 10 | 18 | 2
General
Asthenia |  | 33 | 4 | 23 | 4
Fatigue |  | 31 | 6 | 27 | 4
Edema peripheral |  | 25 | <1 | 8 | <1
Pyrexia |  | 20 | <1 | 9 | 0
Mucosal inflammation |  | 19 | 2 | 1 | 0
Respiratory, Thoracic and Mediastinal
Cough |  | 30 | <1 | 16 | 0
Dyspnea |  | 24 | 8 | 15 | 3
Epistaxis |  | 18 | 0 | 0 | 0
Pneumonitis [Includes pneumonitis, interstitial lung disease, lung infiltration, pulmonary alveolar hemorrhage, pulmonary toxicity, and alveolitis.] |  | 14 | 4^4 | 0 | 0
Skin and Subcutaneous Tissue
Rash |  | 29 | 1 | 7 | 0
Pruritus |  | 14 | < 1 | 7 | 0
Dry skin |  | 13 | < 1 | 5 | 0
Metabolism and Nutrition
Anorexia |  | 25 | 2 | 14 | <1
Nervous System
Headache |  | 19 | 1 | 9 | <1
Dysgeusia |  | 10 | 0 | 2 | 0
Musculoskeletal and Connective Tissue
Pain in extremity |  | 10 | 1 | 7 | 0
Grading according to NCI CTCAE Version 3.0.

Other notable adverse reactions occurring more frequently with Everolimus than with placebo, but with an incidence of <10% include:

Gastrointestinal: Abdominal pain (9%), dry mouth (8%), hemorrhoids (5%), dysphagia (4%)
General: Weight loss (9%), chest pain (5%), chills (4%), impaired wound healing (<1%)
Respiratory, Thoracic and Mediastinal: Pleural effusion (7%), pharyngolaryngeal pain (4%), rhinorrhea (3%)
Skin and Subcutaneous Tissue: Hand-foot syndrome (reported as palmar-plantar erythrodysesthesia syndrome) (5%), nail disorder (5%), erythema (4%), onychoclasis (4%), skin lesion (4%), acneiform dermatitis (3%), angioedema (<1%)
Metabolism and Nutrition: Exacerbation of pre-existing diabetes mellitus (2%), new onset of diabetes mellitus (<1%)
Psychiatric: Insomnia (9%)
Nervous System: Dizziness (7%), paresthesia (5%)
Ocular: Eyelid edema (4%), conjunctivitis (2%)
Vascular: Hypertension (4%), deep vein thrombosis (<1%)
Renal and Urinary: Renal failure (3%)
Cardiac: Tachycardia (3%), congestive cardiac failure (1%)
Musculoskeletal and Connective Tissue: Jaw pain (3%)
Hematologic: Hemorrhage (3%)

Table 13: Selected Laboratory Abnormalities Reported in Patients with RCC at a Higher Rate in the Everolimus Arm Than the Placebo Arm in RECORD-1
Laboratory Parameter | Everolimus N = 274 |  | Placebo N = 137
 | All Grades | Grade 3-4 | All Grades | Grade 3-4
 | % | % | % | %
Hematology [Reflects corresponding adverse drug reaction reports of anemia, leukopenia, lymphopenia, neutropenia, and thrombocytopenia (collectively pancytopenia), which occurred at lower frequency.]
Anemia | 92 | 13 | 79 | 6
Lymphopenia | 51 | 18 | 28 | 5 [No Grade 4 laboratory abnormalities were reported.]
Thrombocytopenia | 23 | 1 | 2 | < 1
Neutropenia | 14 | < 1 | 4 | 0
Chemistry
Hypercholesterolemia | 77 | 4 | 35 | 0
Hypertriglyceridemia | 73 | < 1 | 34 | 0
Hyperglycemia | 57 | 16 | 25 | 2
Increased creatinine increased | 50 | 2 | 34 | 0
Hypophosphatemia | 37 | 6 | 8 | 0
Increased AST | 25 | 1 | 7 | 0
Increased ALT | 21 | 1 | 4 | 0
Hyperbilirubinemia | 3 | 1 | 2 | 0
Grading according to NCI CTCAE Version 3.0.

Tuberous Sclerosis Complex (TSC)-Associated Renal Angiomyolipoma

The data described below are based on a randomized (2:1), double-blind, placebo-controlled trial (EXIST-2) of Everolimus in 118 patients with renal angiomyolipoma as a feature of TSC (n = 113) or sporadic lymphangioleiomyomatosis (n = 5). The median age of patients was 31 years (18 to 61 years), 89% were white, and 34% were male. The median duration of blinded study treatment was 48 weeks (2 to 115 weeks) for patients receiving Everolimus.

The most common adverse reaction reported for Everolimus (incidence ≥ 30%) was stomatitis. The most common Grade 3 to 4 adverse reactions (incidence ≥ 2%) were stomatitis and amenorrhea. The most common laboratory abnormalities (incidence ≥ 50%) were hypercholesterolemia, hypertriglyceridemia, and anemia. The most common Grade 3 to 4 laboratory abnormality (incidence ≥ 3%) was hypophosphatemia.

The rate of adverse reactions resulting in permanent discontinuation was 3.8% in the Everolimus-treated patients. Adverse reactions leading to permanent discontinuation in the Everolimus arm were hypersensitivity/angioedema/bronchospasm, convulsion, and hypophosphatemia. Dose adjustments (interruptions or reductions) due to adverse reactions occurred in 52% of Everolimus-treated patients. The most common adverse reaction leading to Everolimus dose adjustment was stomatitis.

Adverse reactions reported with an incidence of ≥ 10% for patients receiving Everolimus and occurring more frequently with Everolimus than with placebo are presented in Table 14. Laboratory abnormalities are presented in Table 15.

Table 14: Adverse Reactions Reported in ≥ 10% of Everolimus-Treated Patients with TSC-Associated Renal Angiomyolipoma in EXIST-2

 | Everolimus; N = 79 |  | Placebo; N = 39
 | All Grades | Grade 3-4 | All Grades | Grade 3-4
 | % | % | % | %
Gastrointestinal
Stomatitis | 78 | 6 [No Grade 4 adverse reactions were reported] | 23 | 0
[Includes stomatitis, aphthous stomatitis, mouth ulceration, gingival pain, glossitis, and glossodynia.] Vomiting | 15 | 0 | 5 | 0
Diarrhea | 14 | 0 | 5 | 0
General
Peripheral edema | 13 | 0 | 8 | 0
Infections
Upper respiratory tract infection | 11 | 0 | 5 | 0
Musculoskeletal and Connective Tissue
Arthralgia | 13 | 0 | 5 | 0
Respiratory, Thoracic and Mediastinal
Cough | 20 | 0 | 13 | 0
Skin and Subcutaneous Tissue
Acne | 22 | 0 | 5 | 0
Grading according to NCI CTCAE Version 3.0

Amenorrhea occurred in 15% of Everolimus-treated females (8 of 52). Other adverse reactions involving the female reproductive system were menorrhagia (10%), menstrual irregularities (10%), and vaginal hemorrhage (8%).

The following additional adverse reactions occurred in less than 10% of Everolimus-treated patients: epistaxis (9%), decreased appetite (6%), otitis media (6%), depression (5%), abnormal taste (5%), increased blood luteinizing hormone (LH) levels (4%), increased blood follicle stimulating hormone (FSH) levels (3%), hypersensitivity (3%), ovarian cyst (3%), pneumonitis (1%), and angioedema (1%).

Table 15: Selected Laboratory Abnormalities Reported in Everolimus-Treated Patients with TSC-Associated Renal Angiomyolipoma in EXIST-2

 | Everolimus; N = 79 |  | Placebo; N = 39
 | All Grades | Grade 3-4 | All Grades | Grade 3-4
 | % | % | % | %
Hematology
Anemia | 61 | 0 | 49 | 0
Leukopenia | 37 | 0 | 21 | 0
Neutropenia | 25 | 1 | 26 | 0
Lymphopenia | 20 | 1 [No Grade 4 laboratory abnormalities were reported.] | 8 | 0
Thrombocytopenia | 19 | 0 | 3 | 0
Chemistry
Hypercholesterolemia | 85 | 1 | 46 | 0
Hypertriglyceridemia | 52 | 0 | 10 | 0
Hypophosphatemia | 49 | 5 | 15 | 0
Increased alkaline phosphatase | 32 | 1 | 10 | 0
Increased AST | 23 | 1 | 8 | 0
Increased ALT | 20 | 1 | 15 | 0
Hyperglycemia (fasting) | 14 | 0 | 8 | 0
Grading according to NCI CTCAE Version 3.0

Updated safety information from 112 patients treated with Everolimus for a median duration of 3.9 years identified the following additional adverse reactions and selected laboratory abnormalities: increased partial thromboplastin time (63%), increased prothrombin time (40%), decreased fibrinogen (38%), urinary tract infection (31%), proteinuria (18%), abdominal pain (16%), pruritus (12%), gastroenteritis (12%), myalgia (11%), and pneumonia (10%).

6.2 Postmarketing Experience

The following adverse reactions have been identified during postapproval use of Everolimus. Because these reactions are reported voluntarily from a population of uncertain size, it is not always possible to reliably estimate frequency or establish a causal relationship to drug exposure:

- Blood and lymphatic disorders: Thrombotic microangiopathy
- Cardiac: Cardiac failure with some cases reported with pulmonary hypertension (including pulmonary arterial hypertension) as a secondary event
- Gastrointestinal: Acute pancreatitis
- Hepatobiliary: Cholecystitis and cholelithiasis
- Infections: Sepsis and septic shock
- Nervous System: Reflex sympathetic dystrophy
- Vascular: Arterial thrombotic events, lymphedema
- Injury, poisoning and procedural complications: Radiation Sensitization and Radiation Recall

7 DRUG INTERACTIONS

7.1 Effect of Other Drugs on Everolimus

Inhibitors

Avoid the concomitant use of P-gp and strong CYP3A4 inhibitors [see Dosage and Administration (2.11), Clinical Pharmacology (12.3)].

Reduce the dose for patients taking Everolimus with a P-gp and moderate CYP3A4 inhibitor as recommended [see Dosage and Administration (2.11), Clinical Pharmacology (12.3)].

Inducers

Increase the dose for patients taking Everolimus with a P-gp and strong CYP3A4 inducer as recommended [see Dosage and Administration (2.12), Clinical Pharmacology (12.3)].

7.2 Effects of Combination Use of Angiotensin Converting Enzyme (ACE) Inhibitors

Patients taking concomitant ACE inhibitors with Everolimus may be at increased risk for angioedema. Avoid the concomitant use of ACE inhibitors with Everolimus [see Warnings and Precautions (5.4)].

8 USE IN SPECIFIC POPULATIONS

8.1 Pregnancy

Risk Summary

Based on animal studies and the mechanism of action [see Clinical Pharmacology (12.1)], Everolimus can cause fetal harm when administered to a pregnant woman. There are limited case reports of Everolimus use in pregnant women; however, these reports are not sufficient to inform about risks of birth defects or miscarriage. In animal studies, everolimus caused embryo-fetal toxicities in rats when administered during the period of organogenesis at maternal exposures that were lower than human exposures at the recommended dose of Everolimus 10 mg orally once daily [see Data]. Advise pregnant women of the potential risk to the fetus.

In the U.S. general population, the estimated background risk of major birth defects and miscarriage is 2% to 4% and 15% to 20% of clinically recognized pregnancies, respectively.

Data

Animal Data: In animal reproductive studies, oral administration of everolimus to female rats before mating and through organogenesis induced embryo-fetal toxicities, including increased resorption, pre-implantation and post-implantation loss, decreased numbers of live fetuses, malformation (e.g., sternal cleft), and retarded skeletal development. These effects occurred in the absence of maternal toxicities. Embryo-fetal toxicities in rats occurred at doses ≥0.1 mg/kg (0.6 mg/m^2) with resulting exposures of approximately 4% of the human exposure at the recommended dose of Everolimus 10 mg orally once daily based on area under the curve (AUC). In rabbits, embryo-toxicity evident as an increase in resorptions occurred at an oral dose of 0.8 mg/kg (9.6 mg/m^2). The effect in rabbits occurred in the presence of maternal toxicities.

In a pre- and post-natal development study in rats, animals were dosed from implantation through lactation. At the dose of ≥0.1 mg/kg (0.6 mg/m^2), there were no adverse effects on delivery and lactation or signs of maternal toxicity; however, there were reductions in body weight (up to 9% reduction from the control) and in survival of offspring (~5% died or missing). There were no drug-related effects on the developmental parameters (morphological development, motor activity, learning, or fertility assessment) in the offspring.

8.2 Lactation

Risk Summary

There are no data on the presence of everolimus or its metabolites in human milk, the effects of everolimus on the breastfed infant or on milk production. Everolimus and its metabolites passed into the milk of lactating rats at a concentration 3.5 times higher than in maternal serum. Because of the potential for serious adverse reactions in breastfed infants from everolimus, advise women not to breastfeed during treatment with Everolimus and for 2 weeks after the last dose.

8.3 Females and Males of Reproductive Potential

Pregnancy Testing

Verify the pregnancy status of females of reproductive potential prior to starting Everolimus [see Use in Specific Populations (8.1)].

Contraception

Everolimus can cause fetal harm when administered to pregnant women [see Use in Specific Populations (8.1)].

Females: Advise female patients of reproductive potential to use effective contraception during treatment with Everolimus and for 8 weeks after the last dose.

Males: Advise male patients with female partners of reproductive potential to use effective contraception during treatment with Everolimus and for 4 weeks after the last dose.

Infertility

Females: Menstrual irregularities, secondary amenorrhea, and increases in luteinizing hormone (LH) and follicle stimulating hormone (FSH) occurred in female patients taking Everolimus. Based on these findings, Everolimus may impair fertility in female patients [see Adverse Reactions (6.1) and Nonclinical Toxicology (13.1)].

Males: Cases of reversible azoospermia have been reported in male patients taking Everolimus. In male rats, sperm motility, sperm count, plasma testosterone levels and fertility were diminished at AUC similar to those of the clinical dose of Everolimus 10 mg orally once daily. Based on these findings, Everolimus may impair fertility in male patients [see Nonclinical Toxicology (13.1)].

8.4 Pediatric Use

The safety and effectiveness of Everolimus in pediatric patients have not been established in:

- Renal Cell Carcinoma (RCC)
- TSC-associated renal angiomyolipoma

8.5 Geriatric Use

In RECORD-1, 41% of patients with renal cell carcinoma treated with Everolimus were ≥ 65 years of age, while 7% were ≥ 75 years of age. No overall differences in safety or effectiveness were observed between elderly and younger patients.

8.6 Hepatic Impairment

Everolimus exposure may increase in patients with hepatic impairment [see Clinical Pharmacology (12.3)].

For patients with RCC and TSC-associated renal angiomyolipoma who have hepatic impairment, reduce the Everolimus dose as recommended [see Dosage and Administration (2.10)].

11 DESCRIPTION

Everolimus is a kinase inhibitor.

The chemical name of everolimus is (1R,9S,12S,15R,16E,18R,19R,21R,23S,24E,26E,28E,30S,32S,35R)-1,18-dihydroxy-12-{(1R)-2-[(1S,3R,4R)-4-(2-hydroxyethoxy)-3-methoxycyclohexyl]-1-methylethyl}-19,30-dimethoxy-15,17,21,23,29,35-hexamethyl-11,36-dioxa-4-aza-tricyclo[30.3.1.0^4,9]-hexatriaconta-16,24,26,28-tetraene-2,3,10,14,20-pentaone.

The molecular formula is C53H83NO14 and the molecular weight is 958.22 g/mol. The structural formula is:

Everolimus tablets for oral administration contains 2.5 mg, 5 mg, 7.5 mg, or 10 mg of everolimus, USP and the following inactive ingredients: anhydrous lactose, butylated hydroxytoluene, crospovidone, hypromellose, and magnesium stearate.

12 CLINICAL PHARMACOLOGY

12.1 Mechanism of Action

Everolimus is an inhibitor of mammalian target of rapamycin (mTOR), a serine-threonine kinase, downstream of the PI3K/AKT pathway. The mTOR pathway is dysregulated in several human cancers and in tuberous sclerosis complex (TSC). Everolimus binds to an intracellular protein, FKBP-12, resulting in an inhibitory complex formation with mTOR complex 1 (mTORC1) and thus inhibition of mTOR kinase activity. Everolimus reduced the activity of S6 ribosomal protein kinase (S6K1) and eukaryotic initiation factor 4E-binding protein (4E-BP1), downstream effectors of mTOR, involved in protein synthesis. S6K1 is a substrate of mTORC1 and phosphorylates the activation domain 1 of the estrogen receptor which results in ligand-independent activation of the receptor. In addition, everolimus inhibited the expression of hypoxia-inducible factor (e.g., HIF-1) and reduced the expression of vascular endothelial growth factor (VEGF). Inhibition of mTOR by everolimus has been shown to reduce cell proliferation, angiogenesis, and glucose uptake in in vitro and/or in vivo studies.

Two regulators of mTORC1 signaling are the oncogene suppressors tuberin-sclerosis complexes 1 and 2 (TSC1, TSC2). Loss or inactivation of either TSC1 or TSC2 leads to activation of downstream signaling. In TSC, a genetic disorder, inactivating mutations in either the TSC1 or the TSC2 gene lead to hamartoma formation throughout the body as well as seizures and epileptogenesis. Overactivation of mTOR results in neuronal dysplasia, aberrant axonogenesis and dendrite formation, increased excitatory synaptic currents, reduced myelination, and disruption of the cortical laminar structure causing abnormalities in neuronal development and function.

12.2 Pharmacodynamics

Cardiac Electrophysiology

In a randomized, placebo-controlled, cross-over study, 59 healthy subjects were administered a single oral dose of Everolimus (20 mg and 50 mg) and placebo. Everolimus at single doses up to 50 mg did not prolong the QT/QTc interval.

12.3 Pharmacokinetics

Absorption

After administration of Everolimus tablets in patients with advanced solid tumors, peak everolimus concentrations are reached 1 to 2 hours after administration of oral doses ranging from 5 mg to 70 mg. Following single doses, Cmax is dose-proportional with daily dosing between 5 mg and 10 mg. With single doses of 20 mg and higher, the increase in Cmax is less than dose-proportional; however, AUC shows dose-proportionality over the 5 mg to 70 mg dose range. Steady-state was achieved within 2 weeks following once-daily dosing.

Effect of Food: In healthy subjects, a high-fat meal (containing approximately 1000 calories and 55 grams of fat) reduced systemic exposure to Everolimus 10 mg (as measured by AUC) by 22% and the peak blood concentration Cmax by 54%. Light-fat meals (containing approximately 500 calories and 20 grams of fat) reduced AUC by 32% and Cmax by 42%.

Distribution

The blood-to-plasma ratio of everolimus, which is concentration-dependent over the range of 5 to 5000 ng/mL, is 17% to 73%. The amount of everolimus confined to the plasma is approximately 20% at blood concentrations observed in cancer patients given Everolimus 10 mg orally once daily. Plasma protein binding is approximately 74% both in healthy subjects and in patients with moderate hepatic impairment.

Elimination

The mean elimination half-life of everolimus is approximately 30 hours.

Metabolism:Everolimus is a substrate of CYP3A4. Following oral administration, everolimus is the main circulating component in human blood. Six main metabolites of everolimus have been detected in human blood, including three monohydroxylated metabolites, two hydrolytic ring-opened products, and a phosphatidylcholine conjugate of everolimus. These metabolites were also identified in animal species used in toxicity studies, and showed approximately 100-times less activity than everolimus itself.

Excretion: No specific elimination studies have been undertaken in cancer patients. Following the administration of a 3 mg single dose of radiolabeled everolimus in patients who were receiving cyclosporine, 80% of the radioactivity was recovered from the feces, while 5% was excreted in the urine. The parent substance was not detected in urine or feces.

Specific Populations

No relationship was apparent between oral clearance and age or sex in patients with cancer.

Patients with Renal Impairment: No significant influence of creatinine clearance (25 to 178 mL/min) was detected on oral clearance (CL/F) of everolimus.

Patients with Hepatic Impairment: Compared to normal subjects, there was a 1.8-fold, 3.2-fold, and 3.6-fold increase in AUC for subjects with mild (Child-Pugh class A), moderate (Child-Pugh class B), and severe (Child-Pugh class C) hepatic impairment, respectively. In another study, the average AUC of everolimus in subjects with moderate hepatic impairment (Child-Pugh class B) was twice that found in subjects with normal hepatic function [see Dosage and Administration (2.10), Use in Specific Populations (8.6)].

Race or Ethnicity: Based on a cross-study comparison, Japanese patients had on average exposures that were higher than non-Japanese patients receiving the same dose. Oral clearance (CL/F) is on average 20% higher in black patients than in white patients.

Drug Interaction Studies

Effect of CYP3A4 and P-glycoprotein (P-gp) Inhibitors on Everolimus: Everolimus exposure increased when Everolimus was coadministered with:

- ketoconazole (a P-gp and strong CYP3A4 inhibitor) - Cmax and AUC increased by 3.9- and 15-fold, respectively.
- erythromycin (a P-gp and moderate CYP3A4 inhibitor) - Cmax and AUC increased by 2- and 4.4-fold, respectively.
- verapamil (a P-gp and moderate CYP3A4 inhibitor) - Cmax and AUC increased by 2.3- and 3.5-fold, respectively.

Effect of CYP3A4 and P-gp Inducers on Everolimus: The coadministration of Everolimus with rifampin, a P-gp and strong inducer of CYP3A4, decreased everolimus AUC by 63% and Cmax by 58% compared to Everolimus alone [see Dosage and Administration (2.12)].

Effect of Everolimus on CYP3A4 Substrates: No clinically significant pharmacokinetic interactions were observed between Everolimus and the HMG-CoA reductase inhibitors atorvastatin (a CYP3A4 substrate), pravastatin (a non-CYP3A4 substrate), and simvastatin (a CYP3A4 substrate).

The coadministration of an oral dose of midazolam (sensitive CYP3A4 substrate) with Everolimus resulted in a 25% increase in midazolam Cmax and a 30% increase in midazolam AUC0-inf.

The coadministration of Everolimus with long acting octreotide increased octreotide Cmin by approximately 50%.

Effect of Everolimus on Antiepileptic Drugs (AEDs): Everolimus increased pre-dose concentrations of the carbamazepine, clobazam, oxcarbazepine, and clobazam’s metabolite N-desmethylclobazam by about 10%. Everolimus had no impact on pre-dose concentrations of AEDs that are substrates of CYP3A4 (e.g., clonazepam and zonisamide) or other AEDs, including valproic acid, topiramate, phenobarbital, and phenytoin.

13 NONCLINICAL TOXICOLOGY

13.1 Carcinogenesis, Mutagenesis, Impairment of Fertility

Administration of everolimus for up to 2 years did not indicate oncogenic potential in mice and rats up to the highest doses tested (0.9 mg/kg) corresponding respectively to 3.9 and 0.2 times the estimated human exposure based on AUC at the recommended dose of Everolimus l0 mg orally once daily.

Everolimus was not genotoxic in a battery of in vitro assays (Ames mutation test in Salmonella, mutation test in L5178Y mouse lymphoma cells, and chromosome aberration assay in V79 Chinese hamster cells). Everolimus was not genotoxic in an in vivo mouse bone marrow micronucleus test at doses up to 500 mg/kg/day (1500 mg/m^2/day, approximately 255-fold the recommended dose of Everolimus 10 mg orally once daily, administered as 2 doses, 24 hours apart.

Based on non-clinical findings, Everolimus may impair male fertility. In a 13-week male fertility study in rats, testicular morphology was affected at doses of 0.5 mg/kg and above. Sperm motility, sperm count, and plasma testosterone levels were diminished in rats treated with 5 mg/kg. The exposures at these doses (52 ng•hr/mL and 414 ng•hr/mL, respectively) were within the range of human exposure at the recommended dose of Everolimus 10 mg orally once daily (560 ng●hr/mL) and resulted in infertility in the rats at 5 mg/kg. Effects on male fertility occurred at AUC0-24h values 10% to 81% lower than human exposure at the recommended dose of Everolimus 10 mg orally once daily. After a 10 to 13 week non-treatment period, the fertility index increased from zero (infertility) to 60%.

Oral doses of everolimus in female rats at ≥0.1 mg/kg (approximately 4% the human exposure based on AUC at the recommended dose of Everolimus 10 mg orally once daily) resulted in increased incidence of pre-implantation loss, suggesting that the drug may reduce female fertility.

13.2 Animal Toxicology and/or Pharmacology

In juvenile rat toxicity studies, dose-related delayed attainment of developmental landmarks including delayed eye-opening, delayed reproductive development in males and females and increased latency time during the learning and memory phases were observed at doses as low as 0.15 mg/kg/day.

14 CLINICAL STUDIES

14.3 Renal Cell Carcinoma (RCC)

An international, multi-center, randomized, double-blind trial (RECORD-1, NCT00410124) comparing Everolimus 10 mg once daily and placebo, both in conjunction with BSC, was conducted in patients with metastatic RCC whose disease had progressed despite prior treatment with sunitinib, sorafenib, or both sequentially. Prior therapy with bevacizumab, interleukin 2, or interferon-α was also permitted. Randomization was stratified according to prognostic score and prior anticancer therapy. The major efficacy outcome measure for the trial was PFS evaluated by RECIST, based on a blinded, independent, central radiologic review. After documented radiological progression, patients randomized to placebo could receive open-label Everolimus. Other outcome measures included OS.

In total, 416 patients were randomized 2:1 to receive Everolimus (n=277) or placebo (n=139). Demographics were well balanced between the arms (median age 61 years; 77% male, 88% white, 74% received prior sunitinib or sorafenib, and 26% received both sequentially).

Everolimus was superior to placebo for PFS (Table 23 and Figure 4). The treatment effect was similar across prognostic scores and prior sorafenib and/or sunitinib. Final OS results yield a hazard ratio of 0.90 (95% CI: 0.71, 1.14), with no statistically significant difference between the arms. Planned cross-over from placebo due to disease progression to open-label Everolimus occurred in 80% of the 139 patients and may have confounded the OS benefit.

Table 23: Progression-Free Survival and Objective Response Rate by Central Radiologic Review in RCC in RECORD-1
 | Everolimus N = 277 | Placebo N = 139 | Hazard Ratio (95% CI) | p-value [Log-rank test stratified by prognostic score.]
Median Progression-free Survival; (95% CI) | 4.9 Months; (4.0, 5.5) | 1.9 Months; (1.8, 1.9) | 0.33; (0.25, 0.43) | <0.0001
Objective Response Rate | 2% | 0% | n/a [Not applicable.] | n/a

Figure 4: Kaplan-Meier Curves for Progression-Free Survival in RCC in RECORD-1

14.4 Tuberous Sclerosis Complex (TSC)-Associated Renal Angiomyolipoma

A randomized (2:1), double-blind, placebo-controlled trial (EXIST-2, NCT00790400) of Everolimus was conducted in 118 patients with renal angiomyolipoma as a feature of TSC (n = 113) or sporadic lymphangioleiomyomatosis (n = 5). The key eligibility requirements for this trial were at least one angiomyolipoma of ≥ 3 cm in longest diameter on CT/MRI based on local radiology assessment, no immediate indication for surgery, and age ≥ 18 years. Patients received Everolimus 10 mg or matching placebo orally once daily until disease progression or unacceptable toxicity. CT or MRI scans for disease assessment were obtained at baseline, 12, 24, and 48 weeks and annually thereafter. Clinical and photographic assessment of skin lesions were conducted at baseline and every 12 weeks thereafter until treatment discontinuation. The major efficacy outcome measure was angiomyolipoma response rate based on independent central radiology review, which was defined as a ≥ 50% reduction in angiomyolipoma volume, absence of new angiomyolipoma lesion ≥ 1 cm, absence of kidney volume increase ≥ 20%, and no angiomyolipoma related bleeding of ≥ Grade 2. Key supportive efficacy outcome measures were time to angiomyolipoma progression and skin lesion response rate. The primary analyses of efficacy outcome measures were limited to the blinded treatment period and conducted 6 months after the last patient was randomized. The comparative angiomyolipoma response rate analysis was stratified by use of enzyme-inducing antiepileptic drugs (EIAEDs) at randomization (yes vs. no).

Of the 118 patients enrolled, 79 were randomized to Everolimus and 39 to placebo. The median age was 31 years (18 to 61 years), 34% were male, and 89% were white. At baseline, 17% of patients were receiving EIAEDs. On central radiology review at baseline, 92% of patients had at least 1 angiomyolipoma of ≥ 3 cm in longest diameter, 29% had angiomyolipomas ≥ 8 cm, 78% had bilateral angiomyolipomas, and 97% had skin lesions. The median values for the sum of all target renal angiomyolipoma lesions at baseline were 85 cm^3 (9 to 1612 cm^3) and 120 cm^3 (3 to 4520 cm^3) in the Everolimus and placebo arms, respectively. Forty-six (39%) patients had prior renal embolization or nephrectomy. The median duration of follow-up was 8.3 months (0.7 to 24.8 months) at the time of the primary analysis.

The renal angiomyolipoma response rate was statistically significantly higher in Everolimus-treated patients (Table 24). The median response duration was 5.3+ months (2.3+ to 19.6+ months).

There were 3 patients in the Everolimus arm and 8 patients in the placebo arm with documented angiomyolipoma progression by central radiologic review (defined as a ≥ 25% increase from nadir in the sum of angiomyolipoma target lesion volumes to a value greater than baseline, appearance of a new angiomyolipoma ≥ 1 cm in longest diameter, an increase in renal volume ≥ 20% from nadir for either kidney and to a value greater than baseline, or Grade ≥ 2 angiomyolipoma-related bleeding). The time to angiomyolipoma progression was statistically significantly longer in the Everolimus arm (HR 0.08 [95% CI: 0.02, 0.37]; p < 0.0001).

Table 24: Angiomyolipoma Response Rate in TSC-Associated Renal Angiomyolipoma in EXIST-2

 | Everolimus; N = 79 | Placebo; N = 39 | p-value
Primary analysis
Angiomyolipoma response rate [Per independent central radiology review.] –; % 95% CI | 41.8; (30.8, 53.4) | 0; (0.0, 9.0) | <0.0001

Skin lesion response rates were assessed by local investigators for 77 patients in the Everolimus arm and 37 patients in the placebo arm who presented with skin lesions at study entry. The skin lesion response rate was statistically significantly higher in the Everolimus arm (26% vs. 0, p = 0.0011); all skin lesion responses were partial responses, defined as visual improvement in 50% to 99% of all skin lesions durable for at least 8 weeks (Physician's Global Assessment of Clinical Condition).

Patients randomized to placebo were permitted to receive Everolimus at the time of angiomyolipoma progression or after the time of the primary analysis. After the primary analysis, patients treated with Everolimus underwent additional follow-up CT or MRI scans to assess tumor status until discontinuation of treatment or completion of 4 years of follow-up after the last patient was randomized. A total of 112 patients (79 randomized to Everolimus and 33 randomized to placebo) received at least one dose of Everolimus. The median duration of Everolimus treatment was 3.9 years (0.5 months to 5.3 years) and the median duration of follow-up was 3.9 years (0.9 months to 5.4 years). During the follow-up period after the primary analysis, 32 patients (in addition to the 33 patients identified at the time of the primary analysis) had an angiomyolipoma response based upon independent central radiology review. Among the 65 responders out of 112 patients, the median time to angiomyolipoma response was 2.9 months (2.6 to 33.8 months). Fourteen percent of the 112 patients treated with Everolimus had angiomyolipoma progression by the end of the follow-up period. No patient underwent a nephrectomy for angiomyolipoma progression and one patient underwent renal embolization while treated with Everolimus.

15 REFERENCES

OSHA Hazardous Drugs. OSHA. http://www.osha.gov/SLTC/hazardousdrugs/index.html.

16 HOW SUPPLIED/STORAGE AND HANDLING

Everolimus Tablets

2.5 mg tablets are supplied as a white to off white, uniform to lightly speckled, capsule-shaped, flat-face, beveled edge tablet with “54 [space] 391” debossed on one side and plain on the other side.

NDC 0054-0480-13: Bottle of 30 Tablets

NDC 0054-0480-22: Bottle of 90 Tablets

NDC 0054-0480-14: Blister Pack of 28 Tablets

5 mg tablets are supplied as a white to off white, uniform to lightly speckled, capsule-shaped, flat-face, beveled edge tablet with “54 [space] 451” debossed on one side and plain on the other side.

NDC 0054-0481-13: Bottle of 30 Tablets

NDC 0054-0481-22: Bottle of 90 Tablets

NDC 0054-0481-14: Blister Pack of 28 Tablets

7.5 mg tablets are supplied as a white to off white, uniform to lightly speckled, capsule-shaped, flat-face, beveled edge tablet with “54 [space] 627” debossed on one side and plain on the other side.

NDC 0054-0497-13: Bottle of 30 Tablets
NDC 0054-0497-22: Bottle of 90 Tablets

NDC 0054-0497-14: Blister Pack of 28 Tablets

10 mg tablets are supplied as a white to off white, uniform to lightly speckled, capsule-shaped, flat-face, beveled edge tablet with “54 [space] 701” debossed on one side and plain on the other side.

NDC 0054-0482-13: Bottle of 30 Tablets

NDC 0054-0482-22: Bottle of 90 Tablets

NDC 0054-0482-14: Blister Pack of 28 Tablets

Store at 20° to 25°C (68° to 77°F). [See USP Controlled Room Temperature].

Store in the original container; protect from light and moisture.

Follow special handling and disposal procedures for anticancer pharmaceuticals.^1

17 PATIENT COUNSELING INFORMATION

Advise the patient to read the FDA-approved patient labeling (Patient Information).

Non-infectious Pneumonitis

Advise patients of the risk of developing non-infectious pneumonitis and to immediately report any new or worsening respiratory symptoms to their healthcare provider [see Warnings and Precautions (5.1)].

Infections

Advise patients that they are more susceptible to infections and that they should immediately report any signs or symptoms of infections to their healthcare provider [see Warnings and Precautions (5.2)].

Hypersensitivity Reactions

Advise patients of the risk of clinically significant hypersensitivity reactions and to promptly contact their healthcare provider or seek emergency care for signs of hypersensitivity reaction including rash, itching, hives, difficulty breathing or swallowing, flushing, chest pain, or dizziness [see Contraindications (4), Warnings and Precautions (5.3)].

Angioedema with Concomitant Use of ACE Inhibitors

Advise patients to avoid ACE inhibitors and to promptly contact their healthcare provider or seek emergency care for signs or symptoms of angioedema [see Warnings and Precautions (5.4)].

Stomatitis

Advise patients of the risk of stomatitis and to use alcohol-free mouthwashes during treatment [see Warnings and Precautions (5.5)].

Renal Impairment

Advise patients of the risk of developing kidney failure and the need to monitor their kidney function periodically during treatment [see Warnings and Precautions (5.6)].

Risk of Impaired Wound Healing

Advise patients that Everolimus may impair wound healing. Advise patients to inform their healthcare provider of any planned surgical procedure [see Warnings and Precautions (5.7)].

Metabolic Disorders

Advise patients of the risk of metabolic disorders and the need to monitor glucose and lipids periodically during therapy [see Warnings and Precautions (5.9)].

Myelosuppression

Advise patients of the risk of myelosuppression and the need to monitor CBCs periodically during therapy [see Warnings and Precautions (5.10)].

Risk of Infection or Reduced Immune Response with Vaccination

Advise patients to avoid the use of live vaccines and close contact with those who have received live vaccines [see Warnings and Precautions (5.11)].

Embryo-Fetal Toxicity

Advise females of reproductive potential of the potential risk to a fetus. Advise females of reproductive potential to use effective contraception during treatment and for 8 weeks after the last dose. Advise patients to inform their healthcare provider of a known or suspected pregnancy. Advise males with female partners of reproductive potential to use effective contraception during treatment and for 4 weeks after the last dose [see Warnings and Precautions (5.13) and Use in Specific Populations (8.1,8.3)].

Radiation Sensitization and Radiation Recall

Radiation sensitization and recall can occur in patients treated with radiation prior to, during, or subsequent to everolimus treatment. Advise patients to inform their health care provider if they have had or are planning to receive radiation therapy [see Warning and Precautions (5.12)].

Lactation

Advise women not to breastfeed during treatment with Everolimus and for 2 weeks after the last dose [see Use in Specific Populations (8.2)].

Infertility

Advise males and females of reproductive potential of the potential risk for impaired fertility [see Use in Specific Populations (8.3)].

Distributed by: Hikma

Pharmaceuticals USA Inc.

Berkeley Heights, NJ 07922

C50001080

Revised April 2024

PATIENT INFORMATION

Everolimus Tablets
(e’ ver oh’ li mus)

Read this Patient Information leaflet that comes with Everolimus Tablets before you start taking it and each time you get a refill. There may be new information. This information does not take the place of talking to your healthcare provider about your medical condition or treatment.

What is the most important information I should know about Everolimus Tablets?

Everolimus Tablets can cause serious side effects, including:

1. You may develop lung or breathing problems. In some people lung or breathing problems may be severe and can lead to death. Tell your healthcare provider right away if you have any of these symptoms:
2. New or worsening cough
3. Shortness of breath
4. Chest pain
5. Difficulty breathing or wheezing
2. You may be more likely to develop an infection, such as pneumonia, or a bacterial, fungal or viral infection. Viral infections may include active hepatitis B in people who have had hepatitis B in the past (reactivation). In some people (including adults and children) these infections may be severe and can lead to death. You may need to be treated as soon as possible.

Tell your healthcare provider right away if you have a temperature of 100.5°F or above, chills, or do not feel well.

Symptoms of hepatitis B or infection may include the following:

- Fever
- Chills
- Skin rash
- Joint pain and swelling
- Tiredness
- Loss of appetite
- Nausea
- Pale stools or dark urine
- Yellowing of the skin
- Pain in the upper right side of the stomach
3. Severe allergic reactions. Call your healthcare provider or get medical help right away if you get signs and symptoms of a severe allergic reaction including: rash, itching, hives, flushing, trouble breathing or swallowing, chest pain or dizziness.
4. Possible increased risk for a type of allergic reaction called angioedema, in people who take an Angiotensin-Converting Enzyme (ACE) inhibitor medicine during treatment with Everolimus Tablets. Talk with your healthcare provider before taking Everolimus Tablets if you are not sure if you take an ACE inhibitor medicine. Get medical help right away if you have trouble breathing or develop swelling of your tongue, mouth, or throat during treatment with Everolimus Tablets.
5. Mouth ulcers and sores. Mouth ulcers and sores are common during treatment with everolimus but can also be severe. When you start treatment with everolimus, your healthcare provider may tell you to also start a prescription mouthwash to reduce the likelihood of getting mouth ulcers or sores and to reduce their severity. Follow your healthcare provider’s instructions on how to use this prescription mouthwash. If you develop pain, discomfort, or open sores in your mouth, tell your healthcare provider. Your healthcare provider may tell you to re-start this mouthwash or to use a special mouthwash or mouth gel that does not contain alcohol, peroxide, iodine, or thyme.
6. You may develop kidney failure. In some people this may be severe and can lead to death. Your healthcare provider should do tests to check your kidney function before and during your treatment with Everolimus Tablets.

If you have any of the serious side effects listed above, you may need to stop taking Everolimus Tablets for a while or use a lower dose. Follow your healthcare provider’s instructions.

What are Everolimus Tablets?

Everolimus Tablets are a prescription medicine used to treat:

- Adults with advanced kidney cancer (renal cell carcinoma or RCC) when certain other medicines have not worked.
- people with the following types of tumors that are seen with a genetic condition called tuberous sclerosis complex (TSC):
  - adults with a kidney tumor called angiomyolipoma, when their kidney tumor does not require surgery right away.

It is not known if Everolimus Tablets are safe and effective in children to treat:

- kidney cancer (renal cell carcinoma)
- a kidney tumor called angiomyolipoma, that can happen in children with a genetic condition called tuberous sclerosis complex (TSC).

Do not take Everolimus Tablets if you have had a severe allergic reaction to everolimus.

Talk to your healthcare provider before taking this medicine if you are allergic to:

- a medicine that contains sirolimus
- a medicine that contains temsirolimus
  Ask your healthcare provider if you do not know.

Before taking Everolimus Tablets, tell your healthcare provider about all of your medical conditions, including if you:

- Have or have had kidney problems
- Have or have had liver problems
- Have diabetes or high blood sugar
- Have high blood cholesterol levels
- Have any infections
- Previously had hepatitis B
- Are scheduled to receive any vaccinations. You should not receive a “live vaccine” or be around people who have recently received a “live vaccine” during your treatment with Everolimus Tablets. If you are not sure about the type of immunization or vaccine, ask your healthcare provider.
- Are pregnant, can become pregnant, or have a partner who can become pregnant. Everolimus Tablets can cause harm to your unborn baby.
  Females who are able to become pregnant:
o Your healthcare provider will give you a pregnancy test before you start treatment with Everolimus Tablets.
o You should use effective birth control during treatment and for 8 weeks after your last dose of Everolimus Tablets.
Males with a female partner, you should use effective birth control during treatment and for 4 weeks after your last dose of Everolimus Tablets.
Talk to your healthcare provider about birth control methods that may be right for you during this time. If you become pregnant or think you are pregnant, tell your healthcare provider right away.
- Are breastfeeding or plan to breastfeed. It is not known if Everolimus passes into your breast milk. Do not breastfeed during treatment and for 2 weeks after your last dose of Everolimus Tablets.
- Are planning to have surgery or if you have had a recent surgery. You should stop taking Everolimus Tablets at least 1 week before planned surgery. See “Whatare the possible side effects of Everolimus Tablets?”
- Have received radiation therapy or are planning to receive radiation therapy in the future. See “What are the possible side effects of Everolimus Tablets?

Tell your healthcare provider about all of the medicines you take, including prescription and over-the-counter medicines, vitamins, and herbal supplements.

Everolimus Tablets may affect the way other medicines work, and other medicines can affect how Everolimus Tablets work. Taking Everolimus Tablets with other medicines can cause serious side effects.

Know the medicines you take. Keep a list of them and show it to your healthcare provider and pharmacist when you get a new medicine. Especially tell your healthcare provider if you take:

- St. John’s Wort (Hypericum perforatum)
- Medicine for:
- Fungal infections
- Bacterial infections
- Tuberculosis
- Seizures
- HIV-AIDS
- Heart conditions or high blood pressure
- Medicines that weaken your immune system (your body’s ability to fight infections and other problems)

Ask your healthcare provider or pharmacist if you are not sure if your medicine is one of those taken for the conditions listed above. If you are taking any medicines for the conditions listed above, your healthcare provider might need to prescribe a different medicine or your dose of Everolimus Tablets may need to be changed. You should also tell your healthcare provider before you start taking any new medicine.

How should I take Everolimus Tablets?

- Your healthcare provider will prescribe the dose of Everolimus Tablets that is right for you.
- Take Everolimus Tablets exactly as your healthcare provider tells you to.
- Your healthcare provider may change your dose of Everolimus Tablets or tell you to temporarily interrupt dosing, if needed.
- Use scissors to open the blister pack.
- Take Everolimus Tablets 1 time each day at about the same time.
- Take Everolimus Tablets the same way each time, either with food or without food.
- If you take too much Everolimus Tablets contact your healthcare provider or go to the nearest hospital emergency room right away. Take the bottle or blister pack of Everolimus Tablets with you.
- If you miss a dose of Everolimus Tablets, you may take it if it is less than 6 hours after the time you normally take it. If it is more than 6 hours after you normally take your Everolimus Tablets, skip the dose for that day. The next day, take Everolimus Tablets at your usual time. Do not take 2 doses to make up for a missed dose. If you are not sure about what to do, call your healthcare provider.
- You should have blood tests before you start Everolimus Tablets and as needed during your treatment. These will include tests to check your blood cell count, kidney and liver function, cholesterol, and blood sugar levels.
- Swallow Everolimus Tablets whole with a glass of water. Do not take any tablet that is broken or crushed.

What should I avoid while taking Everolimus Tablets?

You should not drink grapefruit juice or eat grapefruit during your treatment with Everolimus Tablets. It may make the amount of Everolimus in your blood increase to a harmful level.

What are the possible side effects of Everolimus Tablets?

Everolimus Tablets can cause serious side effects, including:

- See “What is the most important information I should know about Everolimus Tablets?” for more information.
- Risk of wound healing problems. Wounds may not heal properly during Everolimus Tablets treatment. Tell your healthcare provider if you plan to have any surgery before starting or during treatment with Everolimus Tablets.
  - You should stop taking Everolimus Tablets at least 1 week before planned surgery.
  - Your healthcare provider should tell you when you may start taking Everolimus Tablets again after surgery.
- Increased blood sugar and fat (cholesterol and triglyceride) levels in the blood. Your healthcare provider should do blood tests to check your fasting blood sugar, cholesterol, and triglyceride levels in the blood before you start and during treatment with Everolimus Tablets.
- Decreased blood cell counts. Everolimus Tablets can cause you to have decreased red blood cells, white blood cells, and platelets. Your healthcare provider should do blood tests to check your blood cell counts before you start and during treatment with Everolimus Tablets.
- Worsening side effects from radiation treatment, that can sometimes be severe. Tell your healthcare provider if you have had or are planning to receive radiation therapy.

The most common side effects of Everolimus Tablets in people with advanced kidney cancer include:

- Infections
- Rash
- Feeling weak or tired
- Diarrhea
- Swelling of arms, hands, feet, ankles, face, or other parts of the body
- Stomach-area (abdominal) pain
- Nausea
- Fever
- Cough
- Headache
- Decreased appetite

The most common side effects of Everolimus Tablets in people who have renal angiomyolipoma with TSC include respiratory tract infections.

Other side effects that may occur with Everolimus Tablets:

- Absence of menstrual periods (menstruation). You may miss 1 or more menstrual periods. Tell your healthcare provider if this happens.
- Everolimus Tablets may affect fertility in females and may affect your ability to become pregnant. Talk to your healthcare provider if this is a concern for you.
- Everolimus Tablets may affect fertility in males and may affect your ability to father a child. Talk to your healthcare provider if this is a concern for you.

Tell your healthcare provider if you have any side effect that bothers you or does not go away.

These are not all the possible side effects of Everolimus Tablets. For more information, ask your healthcare provider or pharmacist.

Call your doctor for medical advice about side effects. You may report side effects to FDA at 1-800-FDA-1088.

How should I store Everolimus Tablets?

- Store Everolimus Tablets at room temperature, between 68° to 77°F (20° to 25°C).
- Keep Everolimus Tablets in the container it comes in.
- Open the blister pack just before taking Everolimus Tablets.
- Keep Everolimus Tablets dry and away from light.
- Do not use Everolimus Tablets that is out of date or no longer needed.

Keep Everolimus Tablets and all medicines out of the reach of children.

General information about the safe and effective use of Everolimus Tablets.

Medicines are sometimes prescribed for purposes other than those listed in a Patient Information leaflet. Do not use Everolimus Tablets for a condition for which it was not prescribed. Do not give Everolimus Tablets to other people, even if they have the same problem you have. It may harm them. This leaflet summarizes the most important information about Everolimus Tablets. If you would like more information, talk with your healthcare provider. You can ask your healthcare provider or pharmacist for information written for healthcare professionals.

What are the ingredients in Everolimus Tablets?

Active ingredient: everolimus, USP.
Inactive ingredients: anhydrous lactose, butylated hydroxytoluene, crospovidone, hypromellose, and magnesium stearate.

This Patient Information has been approved by the U.S. Food and Drug Administration.

The brands listed are the trademarks or register marks of their respective owners and are not trademarks or register marks of Hikma Pharmaceuticals USA Inc.

For more information, call 1-800-962-8364.

Distributed by: Hikma

Pharmaceuticals USA Inc.

Berkeley Heights, NJ 07922

C50001080

Revised April 2024

PACKAGE/LABEL PRINCIPAL DISPLAY PANEL

Everolimus Tablets 2.5 mg 30 Tablets
NDC 0054-0480-13, Rx only

Package/Label Display Panel

Everolimus Tablets 5 mg 30 Tablets
NDC 0054-0481-13, Rx only

Package/Label Display Panel

Everolimus Tablets 7.5 mg 30 Tablets
NDC 0054-0497-13, Rx only

Package/Label Display Panel

Everolimus Tablets, 10 mg 30 Tablets

NDC 0054-0482-13, Rx only